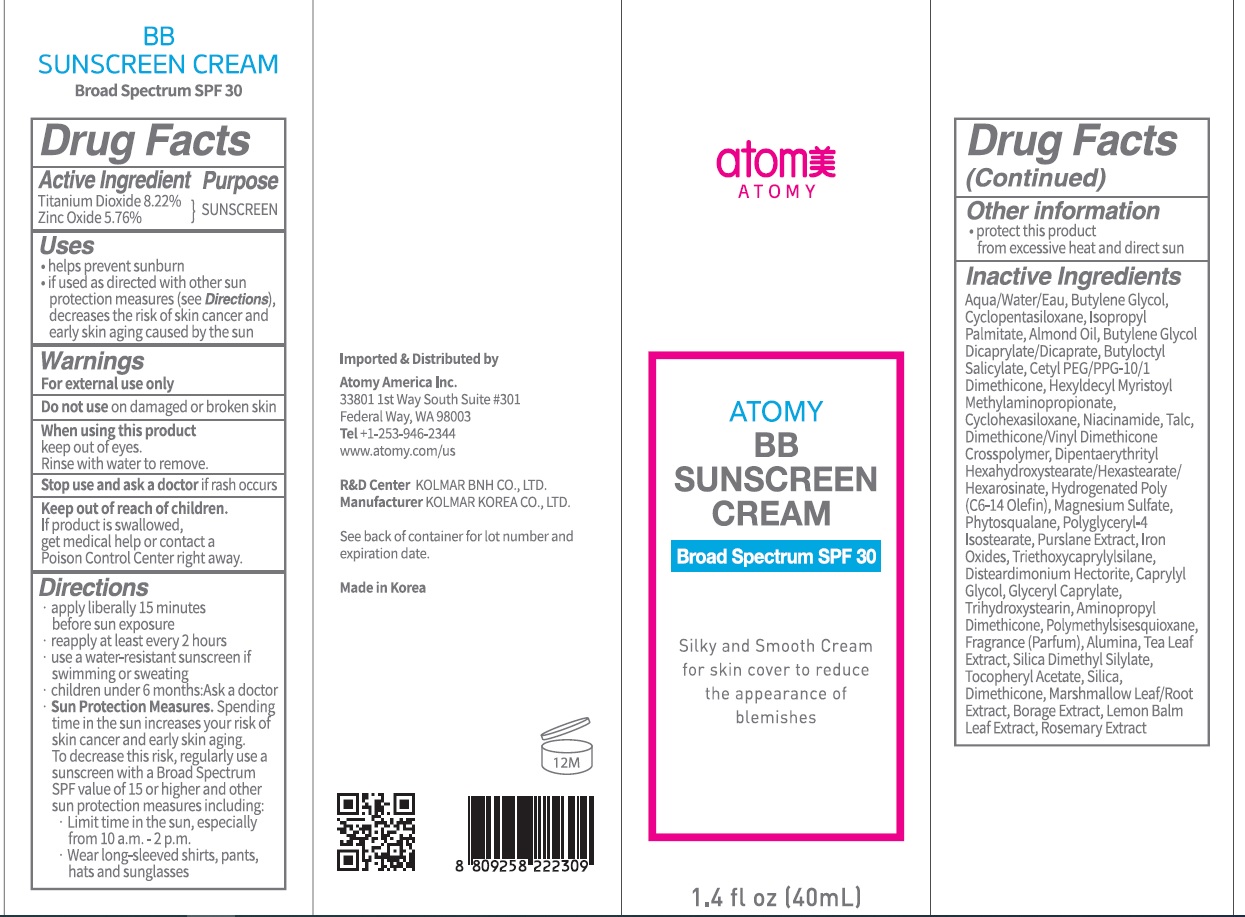 DRUG LABEL: ATOMY BB SUNSCREEN
NDC: 52257-1430 | Form: CREAM
Manufacturer: ATOMY CO., LTD.
Category: otc | Type: HUMAN OTC DRUG LABEL
Date: 20240131

ACTIVE INGREDIENTS: TITANIUM DIOXIDE 8.22 g/100 mL; ZINC OXIDE 5.76 g/100 mL
INACTIVE INGREDIENTS: Water; Butylene Glycol; CYCLOMETHICONE 5

ACTIVE INGREDIENTS

Titanium Dioxide 8.22%
Zinc Oxide 5.76%

INACTIVE INGREDIENTS

Aqua/Water/Eau, Butylene Glycol, Cyclopentasiloxane, Isopropyl Palmitate, Almond Oil, Butylene Glycol Dicaprylate/Dicaprate, Butyloctyl Salicylate, Cetyl PEG/PPG-10/1 Dimethicone, Hexyldecyl Myristoyl Methylaminopropionate, Cyclohexasiloxane, Niacinamide, Talc, Dimethicone/Vinyl Dimethicone Crosspolymer, Dipentaerythrityl Hexahydroxystearate/Hexastearate/Hexarosinate, Hydrogenated Poly(C6-14 Olefin), Magnesium Sulfate, Phytosqualane, Polyglyceryl-4 Isostearate, Purslane Extract, Iron Oxides, Triethoxycaprylylsilane, Disteardimonium Hectorite, Caprylyl Glycol, Glyceryl Caprylate, Trihydroxystearin, Aminopropyl Dimethicone, Polymethylsisesquioxane, Fragrance (Parfum), Alumina, Tea Leaf Extract, Silica Dimethyl Silylate, Tocopheryl Acetate, Silica, Dimethicone, Marshmallow Leaf/Root Extract, Borage Extract, Lemon Balm Leaf Extract, Rosemary Extract

PURPOSE

Sunscreen

WARNINGS

For external use only
Do not use on damaged or broken skin
When using this product keep out of eyes. Rinse with water to remove.
Stop use and ask a doctor if rash occurs

KEEP OUT OF REACH OF CHILDREN

If product is swallowed, get medical help or contact a Poison Control Center right away.

Uses

• Helps prevent sunburn
• If used as directed with other sun protection measures
(see Directions), decreases the risk of skin cancer and early skin aging caused by the sun

Directions

• Apply liberally 15 minutes before sun exposure
• Reapply at least every 2 hours
• Use a water-resistant sunscreen if swimming or sweating
• Children under 6 months: Ask a doctor
• Sun Protection Measures. Spending time in the sun increases your risk of skin cancer and early skin aging. To decrease this risk, regularly use a sunscreen with a Broad Spectrum SPF value of 15 or higher and other sun protection measures including:
• Limit time in the sun, especially from 10 a.m. ‒ 2 p.m.
• Wear long-sleeved shirts, pants, hats, and sunglasses